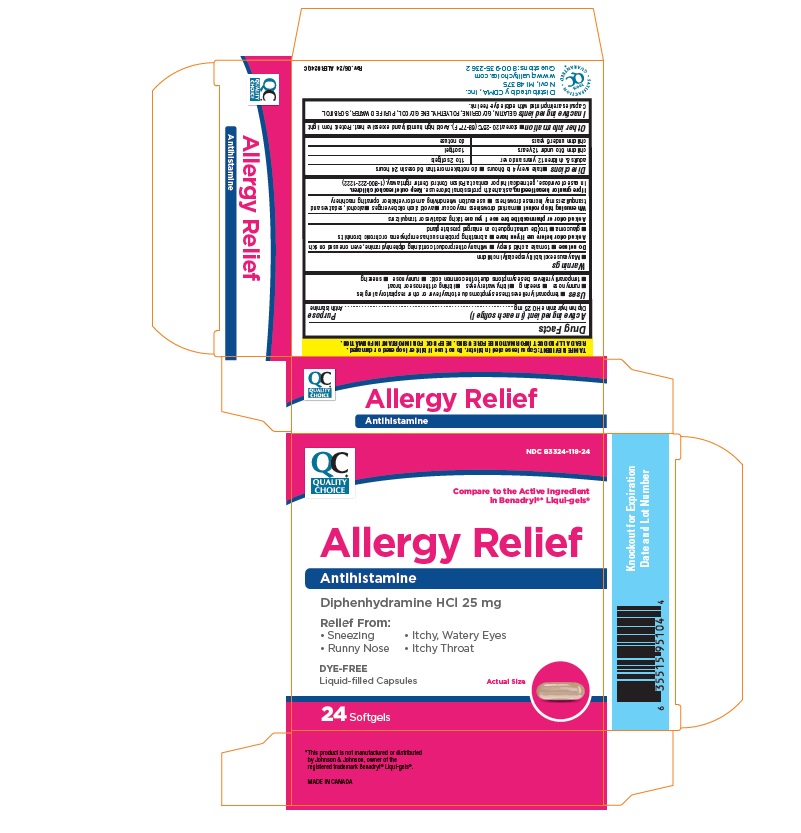 DRUG LABEL: Quality Choice Allergy Relief
NDC: 83324-118 | Form: CAPSULE, LIQUID FILLED
Manufacturer: Chain Drug Marketing Association
Category: otc | Type: HUMAN OTC DRUG LABEL
Date: 20260115

ACTIVE INGREDIENTS: diphenhydramine hydrochloride 25 mg/1 1
INACTIVE INGREDIENTS: gelatin, unspecified; glycerin; polyethylene glycol, unspecified; water; sorbitol

Quality Choice Allergy Relief

Drug Facts

Active ingredient (in each capsule)

Diphenhydramine HCl 25 mg

Purpose

Antihistamine

Uses

- temporarily relieves these symptoms due to hay fever or other upper respiratory allergies:
  - runny nose
  - sneezing
  - itchy, watery eyes
  - itching of the nose or throat
- temporarily relieves these symptoms due to the common cold:
  - runny nose
  - sneezing

Warnings

Do not use

- to make a child sleepy
- with any other product containing diphenhydramine, even one used on skin

Ask a doctor before use if you have

- a breathing problem such as emphysema or chronic bronchitis
- glaucoma
- trouble urinating due to an enlarged prostate gland

Ask a doctor or pharmacist before use if you are taking sedatives or tranquilizers

When using this product

- marked drowsiness may occur
- avoid alcoholic drinks
- alcohol, sedatives, and tranquilizers may increase drowsiness
- be careful when driving a motor vehicle or operating machinery
- excitability may occur, especially in children

PREGNANCY OR BREAST FEEDING

If pregnant or breast-feeding, ask a health professional before use.

Keep out of reach of children. In case of overdose, get medical help or contact a Poison Control Center right away. (1-800-222-1222)

Directions

- take every 4 to 6 hours
- do not take more than 6 doses in 24 hours

adults and children 12 years and over | 1 to 2 capsules
children 6 to under 12 years | 1 capsule
children under 6 years | do not use this product in children under 6 years of age

Other information

- store between 20-25°C (68-77°F). Avoid high humidity and excessive heat. Protect from light.
- do not use if carton is open or blister unit is broken

Inactive ingredients

gelatin, glycerin, polyethylene glycol, purified water, sorbitol. Capsules are imprinted with edible dye-free ink.

Display Panel

DISTRIBUTED BY TOPCO ASSOCIATES LLC
ELK GROVE VILLAGE, IL 60007
©TOPCO RSEA0621 QUESTIONS? 1-888-423-0139 topcare@topco.com www.topcarebrand.com MADE IN CANADA